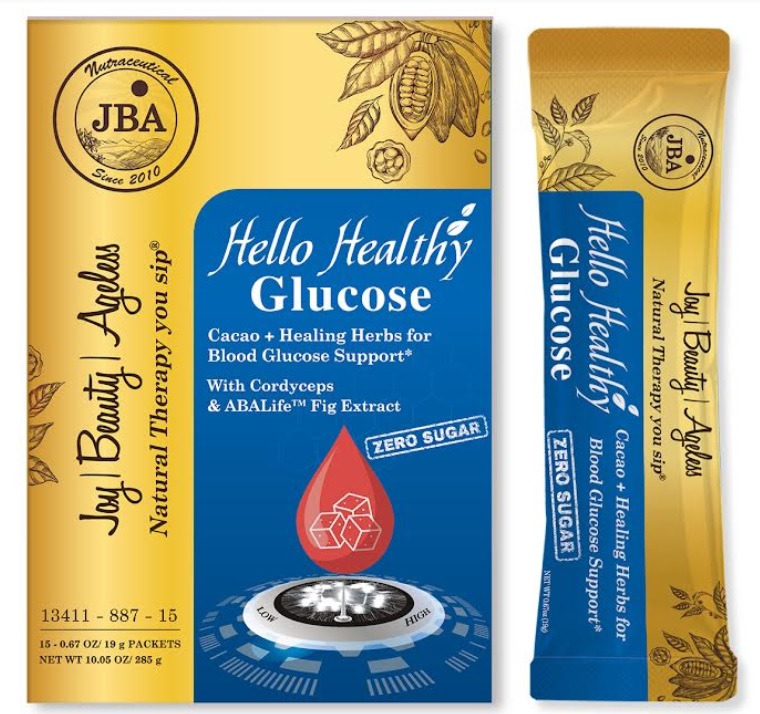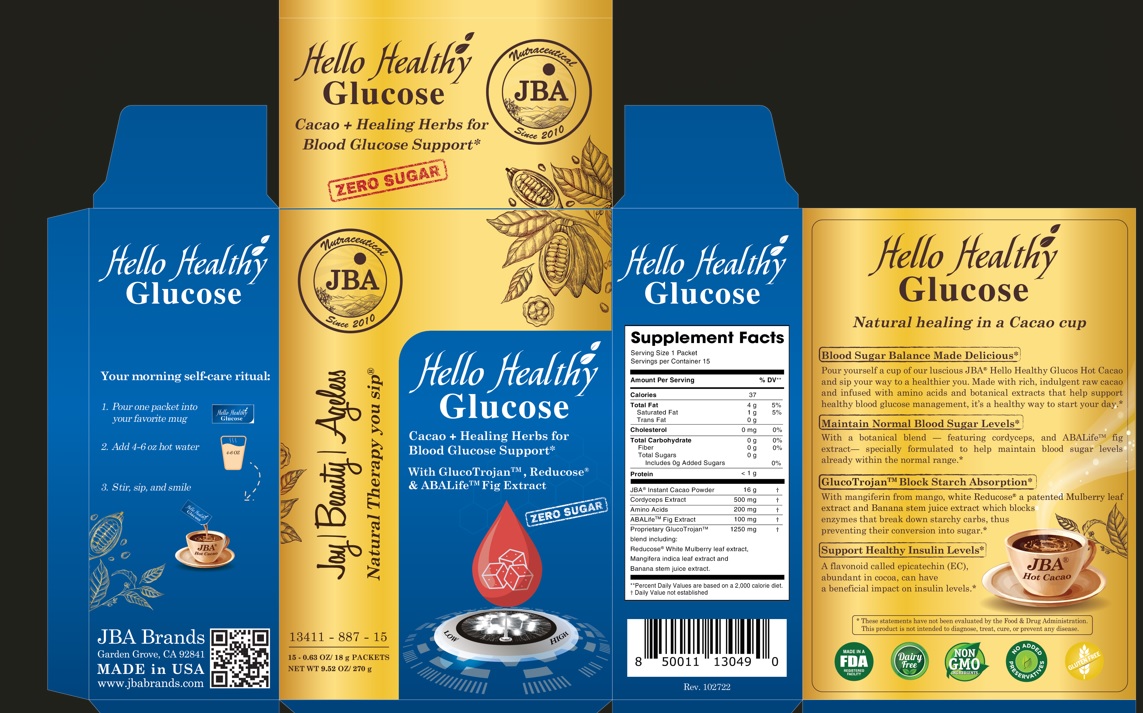 DRUG LABEL: JBA Hello Healthy Glucose Cacao  Healing Herbs for Blood Glucose Support With GlucoTrojan Reducose and ABALife Fig Extract
NDC: 13411-887 | Form: POWDER
Manufacturer: Advanced Pharmaceutical Services, Inc. Dba Affordable Quality Pharmaceuticals
Category: other | Type: DIETARY SUPPLEMENT
Date: 20230220

ACTIVE INGREDIENTS: COCOA 16 g/18 g; OPHIOCORDYCEPS SINENSIS 500 mg/18 g; AMINO ACIDS, SOURCE UNSPECIFIED 200 mg/18 g; CLUSTER FIG 100 mg/18 g; MANGO 500 mg/18 g; BANANA 500 mg/18 g; WHITE MULBERRY 250 mg/18 g

Identity

Dietary supplement

Warnings

Keep out of reach of children
Do not exceed the recommended dose
Consult your physician prior to using this product if you are pregnant, nursing, or if you are taking blood glucose lowering medication, or have a medical condition.

Direction

Your morning self-care ritual:

- Pour one packet into your favorite mug
- Add 4-6 oz hot water
- Stir, sip and smile

Safe handling warning

Store in a cool, dry place

HEALTH CLAIM

JBA® Hello Healthy Glucose
Cacao + Healing Herbs for Blood Glucose Support*
With GlucoTrojan™, Reducose® & ABALife™ Fig Extract

Natural healing in a Cacao cup
Blood Sugar Balance Made Delicious*
Pour yourself a cup or our luscious JBA® Hello Healthy Glucose Hot Cacao and sip your way to a healthier you. Made with rich, indulgent raw cacao and infused with amino acids and botanical extracts that help support blood glucose management, it’s a healthy way to start your day.*

Maintain Normal Blood Sugar Levels*
With a botanical blend – featuring cordyceps, and ABALife™ fig extract – specially formulated to help maintain blood sugar levels already within the normal range.*

GlucoTrojan™ Block Starch Absorption*
With mangiferin from mango, white Reducose® a patented Mulberry leaf extract and Banana stem juice extract which blocks enzymes that break down starchy carbs, thus preventing their conversion into sugar.*

Support Healthy Insulin Levels*
A flavonoid called epicatechin (EC), abundant in cocoa, can have a beneficial impact on insulin levels.*

* These statements have not been evaluated by the Food & Drug Administration. This product is not intended to diagnose, treat, cure, or prevent any disease.